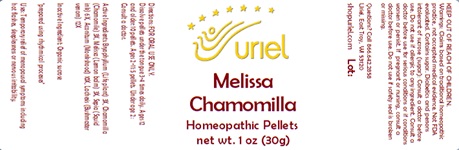 DRUG LABEL: Melissa Chamomilla
NDC: 48951-7152 | Form: PELLET
Manufacturer: Uriel Pharmacy Inc
Category: homeopathic | Type: HUMAN OTC DRUG LABEL
Date: 20240115

ACTIVE INGREDIENTS: MATRICARIA RECUTITA 3 [hp_X]/1 1; MELISSA OFFICINALIS 3 [hp_X]/1 1; ACONITUM NAPELLUS ROOT 10 [hp_X]/1 1; LACHESIS MUTA VENOM 12 [hp_X]/1 1
INACTIVE INGREDIENTS: SUCROSE

Melissa Chamomilla

INDICATIONS AND USAGE

Directions: FOR ORAL USE ONLY.

DOSAGE AND ADMINISTRATION

Dissolve pellets under the tongue 3-4 times daily. Ages 12 and older: 10 pellets. Ages 2-11: 5 pellets. Under age 2: Consult a doctor.

ACTIVE INGREDIENT

Active Ingredients: Bryophyllum (Life plant) 3X, Chamomilla (Chamomile) 3X, Melissa (Lemon balm) 3X, Sepia (Squid ink) 6X, Aconitum (Monkshood) 10X, Lachesis (Bushmaster venom) 12X

Inactive Ingredient: Organic sucrose

"prepared using rhythmical processes"

PURPOSE

Uses: Temporary relief of menopausal symptoms including hot flashes, sleeplessness or nervous irritability.

KEEP OUT OF REACH OF CHILDREN.

WARNINGS

Warnings: Claims based on traditional homeopathic practice, not accepted medical evidence. Not FDA evaluated. Contains sugar. Diabetics and persons intolerant of sucrose (sugar): Consult a doctor before use. Do not use if allergic to any ingredient. Consult a doctor before use for serious conditions or if conditions worsen or persist. If pregnant or nursing, consult a doctor before use. Do not use if safety seal is broken or missing.

Questions? Call 866.642.2858
Uriel, East Troy, WI 53120
shopuriel.com